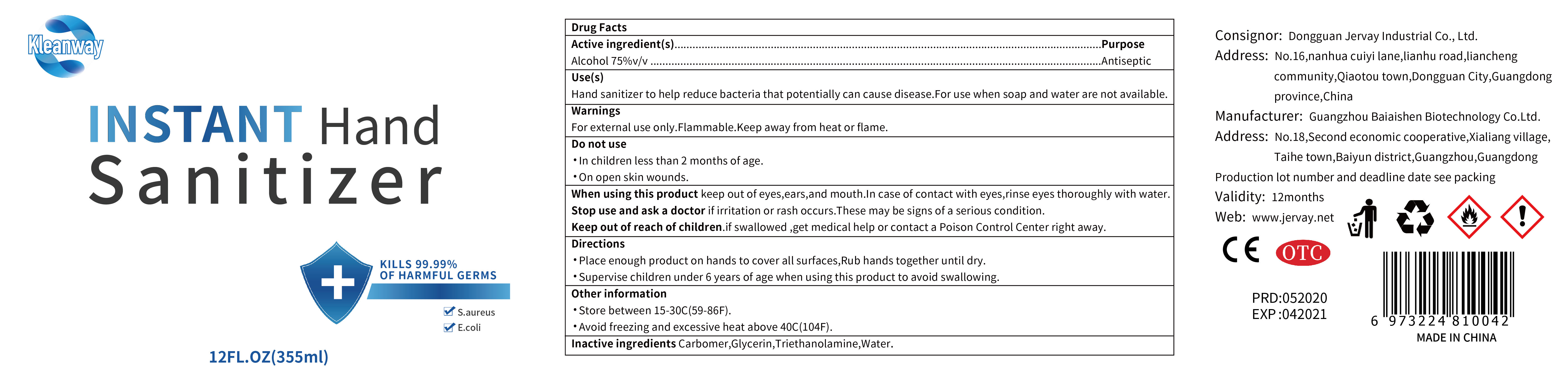 DRUG LABEL: Hand Sanitizer
NDC: 41876-007 | Form: LIQUID
Manufacturer: Dongguan Jervay Industrial Co.,LTD
Category: otc | Type: HUMAN OTC DRUG LABEL
Date: 20200509

ACTIVE INGREDIENTS: ALCOHOL 266.25 mL/355 mL
INACTIVE INGREDIENTS: GLYCERIN; TROLAMINE; WATER; CARBOMER HOMOPOLYMER, UNSPECIFIED TYPE

DOSAGE AND ADMINISTRATION

Store between 15-30C(59-86F).Avoid freezing and excessive heat above 40C(104F).

INACTIVE INGREDIENT

Carbomer

Glycerol

Triethanolamine

Water

INDICATIONS AND USAGE

Place enough product on hands to cover all surfaces,Rub hands together until dry.

ACTIVE INGREDIENT

Alcohol

keep out of children

PURPOSE

Disinfection
Sterilization

WARNINGS

For external use only.Flammable.Keep away from heat or flame.